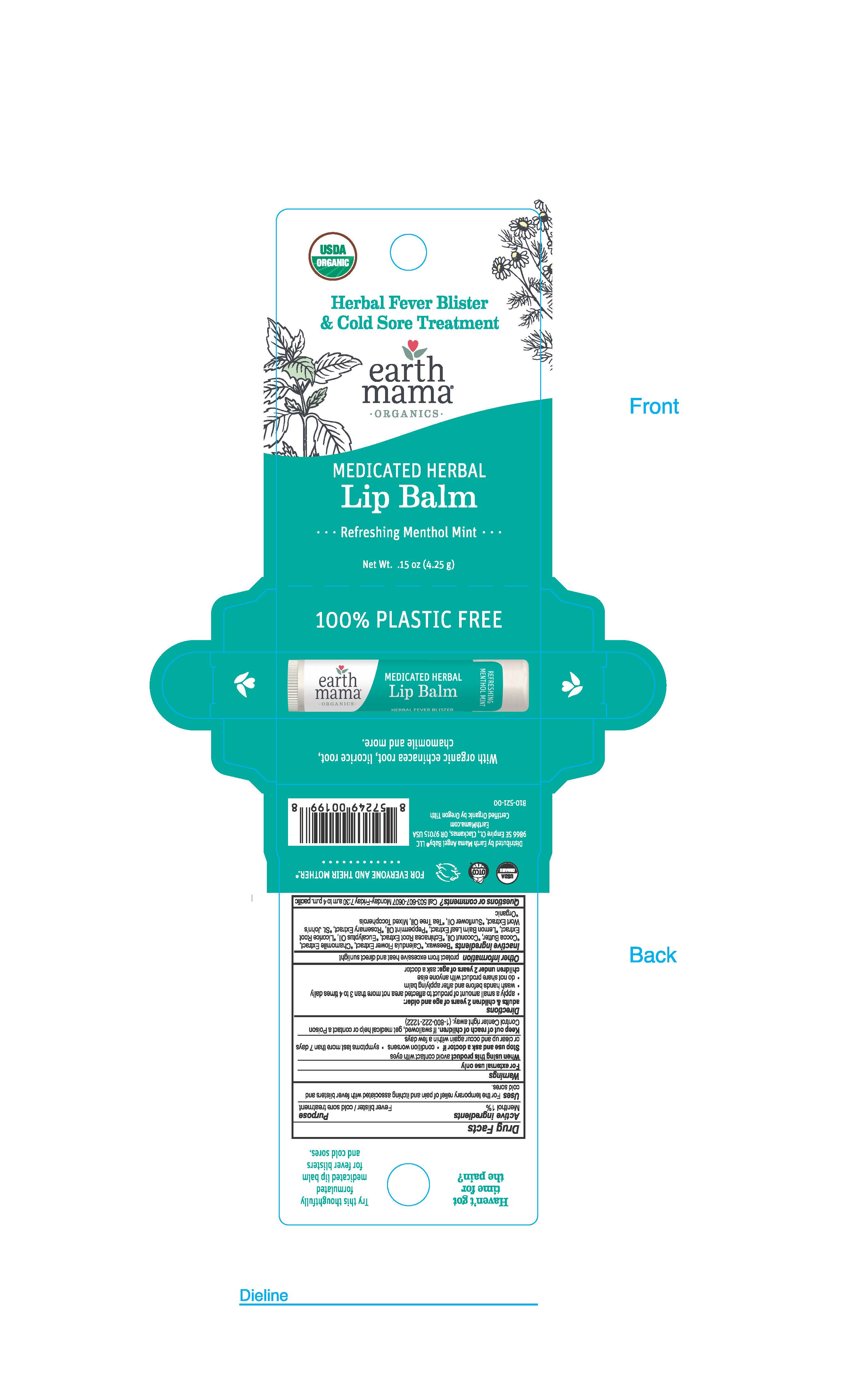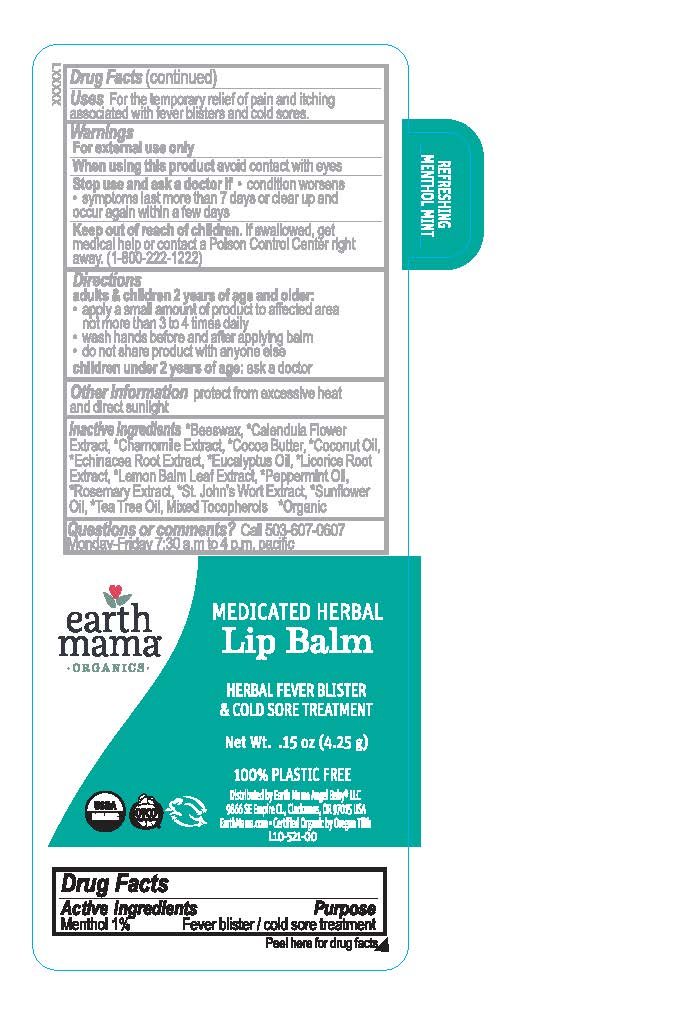 DRUG LABEL: Earth Mama Medicated Herbal Lip Balm
NDC: 79747-155 | Form: STICK
Manufacturer: Eleeo Brands LLC
Category: otc | Type: HUMAN OTC DRUG LABEL
Date: 20250815

ACTIVE INGREDIENTS: MENTHOL 0.0425 g/4.25 g
INACTIVE INGREDIENTS: BEESWAX; EUCALYPTUS OIL; COCONUT OIL; COCOA BUTTER; ROSEMARY OIL; LICORICE; CHAMOMILE FLOWER OIL; PEPPERMINT OIL; LEMON BALM OIL; TOCOPHEROL; CALENDULA OFFICINALIS FLOWER; ST. JOHN'S WORT; TEA TREE OIL; SUNFLOWER OIL; ECHINACEA ANGUSTIFOLIA ROOT

Active Ingredients Menthol 1%

PURPOSE

Fever blister / cold sore treatment

INDICATIONS AND USAGE

For the temporary relief of pain and itching associated with fever blisters and cold sores.

WARNINGS

For external use only When using this productavoid contact with eyes Stop use and ask a doctor if condition worsens symptoms last more than 7 days or clear up and occur again within a few days Keep out of reach of children.If swalowed, get medical help or contact a Poison Control Center right away. (1-800-222-1222)

Keep out of reach of children.If swallowed, get medical help or contact a Poison Control Center right away. (1-800-222-1222)

DOSAGE AND ADMINISTRATION

adults & children 2 years of age and older: apply a smal amount of product to affected area not more than 3 to 4 times daily wash hands before and after applying balm do not share product with anyone else children under 2 years of age:ask a doctor

STORAGE AND HANDLING

Other informationprotect from excessive heat and direct sunlight

INACTIVE INGREDIENT

Inactive ingredients*Beeswax, *Calendula Flower Extract, *Chamomile Extract, *Cocoa Butter, *Coconut Oil, *Echinacea Root Extract, *Eucalyptus Oil, *Licorice Root Extract, *Lemon Balm Leaf Extract, *Peppermint Oil, *Rosemary Extract, *St John's Wort Extract, *Sunflower Oil, *Tea Tree Oil, Mixed Tocopherols. *Organic

Questions or Comments?Cal 503-607-0607 Monday-Friday 7:30 a.m to 4 p.m. pacific

Carton Text Herbal Fever Blister & Cold Sore Treatmentearth mama ORGANICS MEDICATED HERBAL Lip Balm Refreshing Menthol Mint Net Wt 0.15 Oz (4.25 g) 100% PLASTIC FREE Haven't got time for the pain? Try this thoughtfuly formulated medicated lip balm for fever blisters and cold sores. FOR EVERYONE AND THEIR MOTHER Distributed by Eleeo Brands LLC 2150 Winchell Ave. Cincinnati, OH 45214 USA EarthMama.com Certified Organic by Oregon Tilth B10-521-00 With Organic echinacea root, licorice root, chamomile and more.

Label Text earth mama ORGANICS MEDICATED HERBAL Lip Balm HERBAL FEVER BLISTER & COLD SORE TREATMENT Net Wt 0.15 Oz (4.25 g) 100% PLASTIC FREEDistributed by Eleeo Brands 2150 Winchell Ave. Cincinnati, OH 45214 USA EarthMama.com Certified Organic by Oregon Tilth L10-521-00 Refreshing Menthol Mint